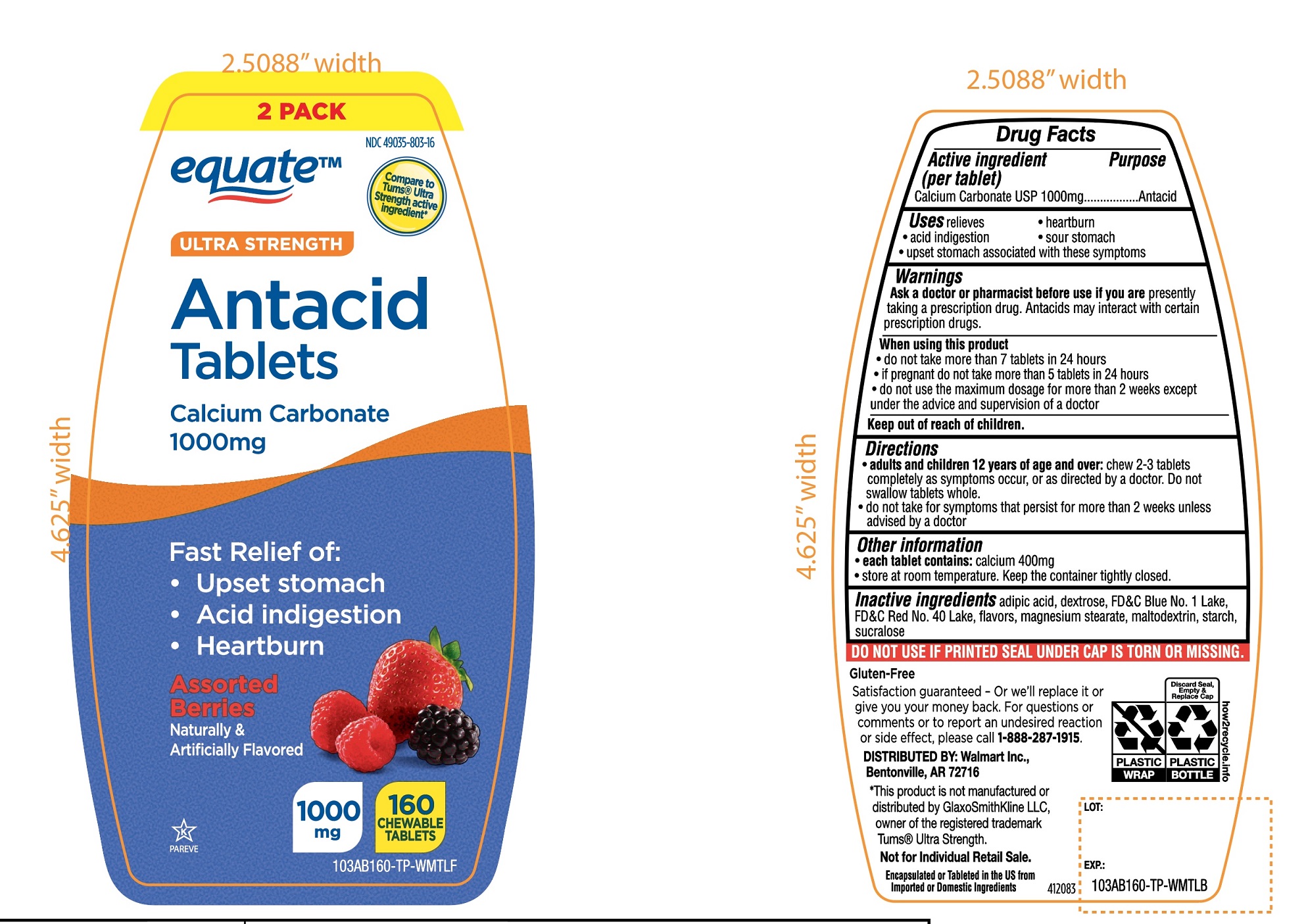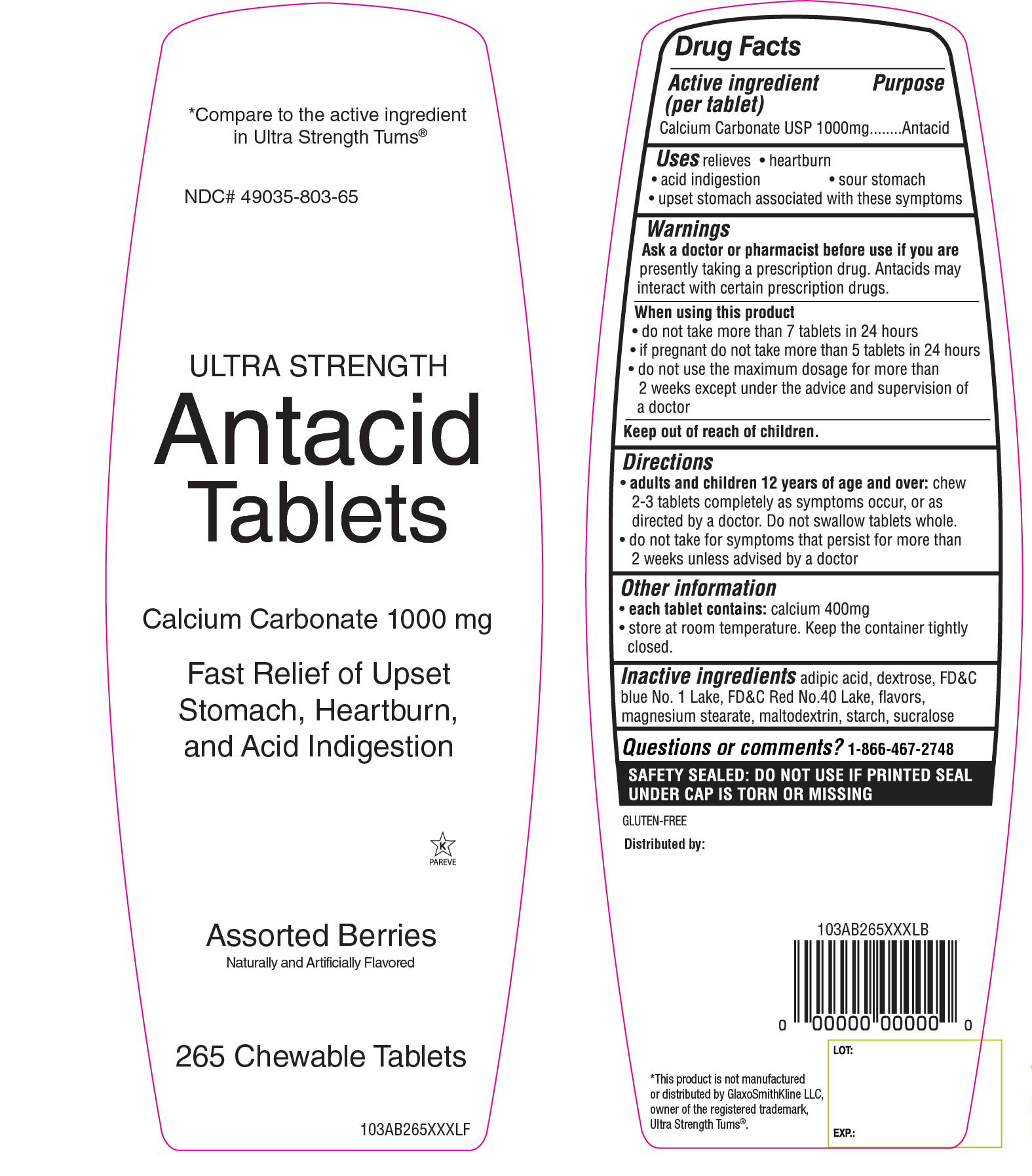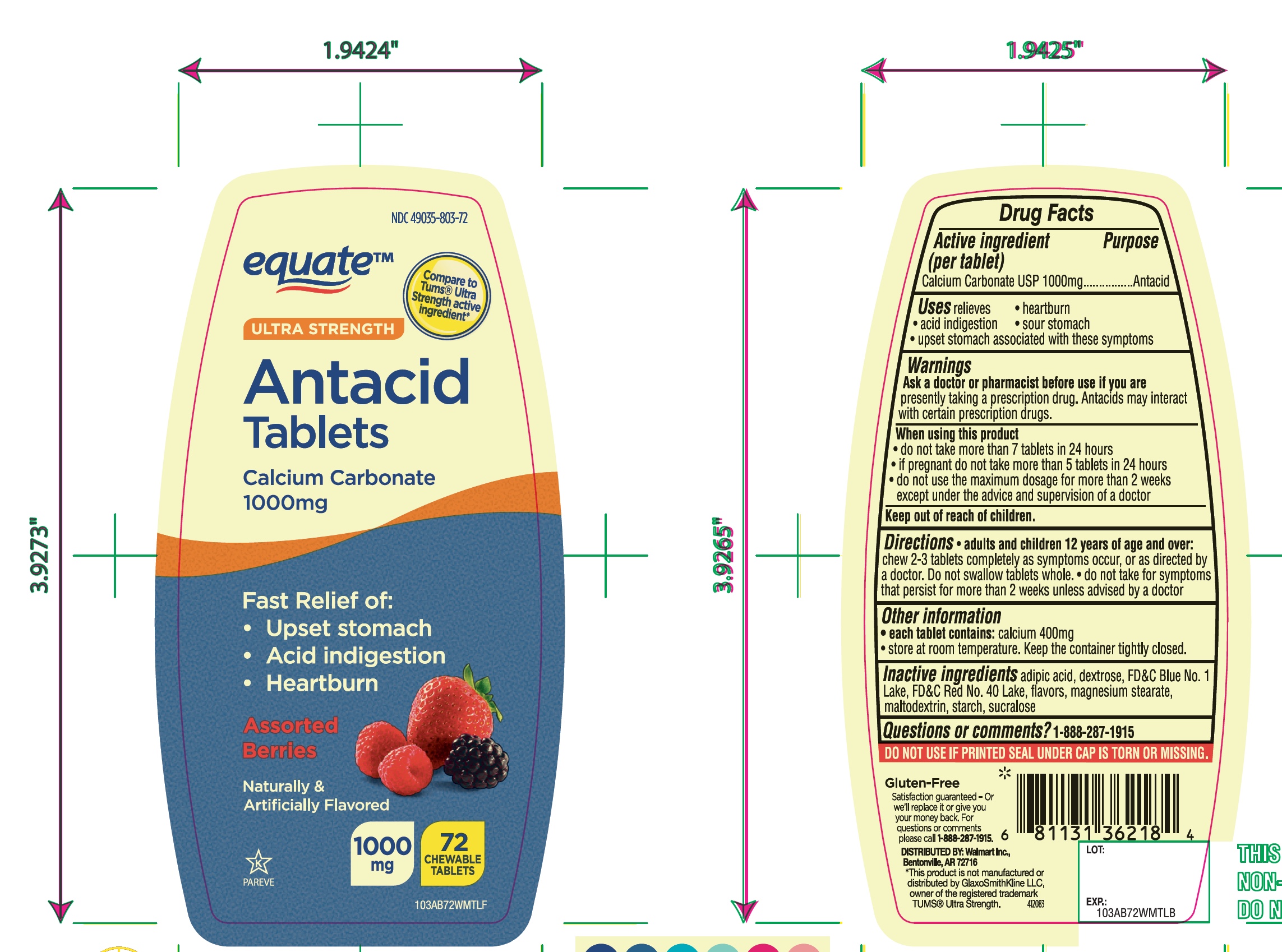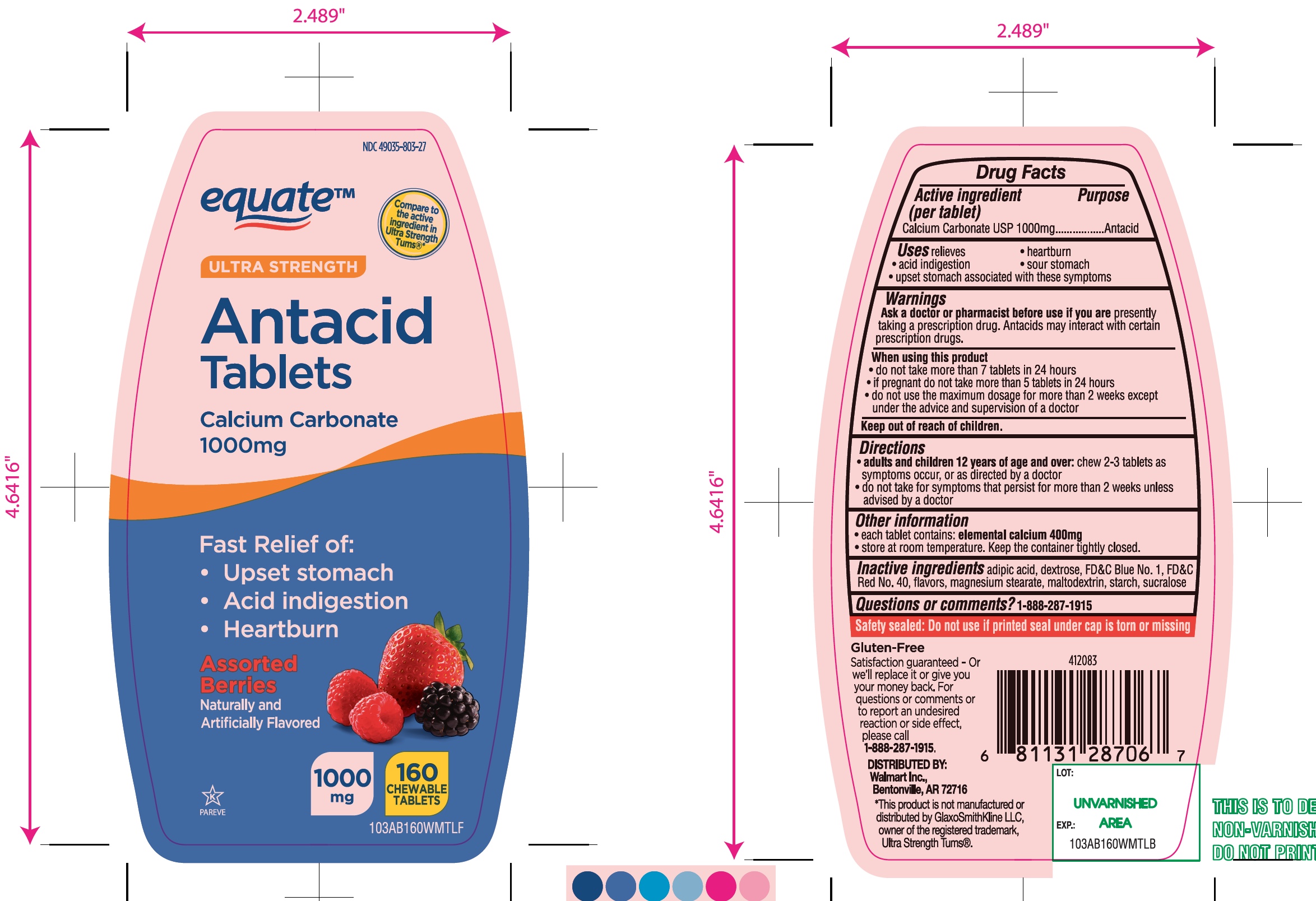 DRUG LABEL: Ultra Strength Antacid
NDC: 49035-803 | Form: TABLET, CHEWABLE
Manufacturer: WAL-MART STORES INC.
Category: otc | Type: HUMAN OTC DRUG LABEL
Date: 20260130

ACTIVE INGREDIENTS: CALCIUM CARBONATE 1000 mg/1 1
INACTIVE INGREDIENTS: ADIPIC ACID; DEXTROSE, UNSPECIFIED FORM; FD&C BLUE NO. 1; FD&C RED NO. 40; MAGNESIUM STEARATE; MALTODEXTRIN; STARCH, CORN; SUCRALOSE

Ultra Strength Antacid Calcium Carbonate Drug Facts

Active ingredient (per tablet)

Calcium Carbonate USP 1000mg

Purpose

Antacid

Uses

relieves

- heartburn
- acid indigestion
- sour stomach
- upset stomach associated with these symptoms

Ask a doctor or pharmacist before use if you are

presently taking a prescription drug. Antacids may interact with certain prescription drugs.

When using this product

- do not take more than 7 tablets in 24 hours
- if pregnant do not take more than 5 tablets in 24 hours
- do not use the maximum dosage for more than 2 weeks except under the advice and supervision of a doctor

Directions

- adults and children 12 years of age and over:chew 2-3 tablets, completely as symptoms occur, or as directed by a doctor. Do not swallow tablets whole.
- do not take for symptoms that persist for more than 2 weeks unless advised by a doctor.

Other information

- each tablet contains:calcium 400mg
- store at room temperature. Keep the container tightly closed.

Inactive ingredients

adipic acid, dextrose, FD&C Blue No. 1 Lake, FD&C Red No. 40 Lake, flavors, magnesium stearate, maltodextrin, starch, sucralose.

Questions or comments?

1-888-287-1915

Safety Sealed

DO NOT USE IF PRINTED SEAL UNDER CAP IS TORN OR MISSING

Package/Label Principal Display Panel

Compare To Tums ®Ultra Strength active ingredient*

ULTRA STRENGTH

Antacid Tablets

Calcium Carbonate 1000 mg

Fast Relief of:

- Upset Stomach
- Acid Indigestion
- Heartburn

Assorted Berries

Naturally and Artificially Flavored

CHEWABLE TABLETS

1000 mg

K PAREVE

Gluten-Free

Satisfaction guaranteed- or we’ll replace it or give you your money back. For questions or comments.

Please call 1-888-287-1915

Distributed By: Walmart Stores, Inc.

Bentonville, AR 72716

*This product is not manufactured or distributed by GlaxoSmithKline LLC, owner of the registered trademark, Ultra Strength Tums ®.

Package Label for 160 Chewable Tablets